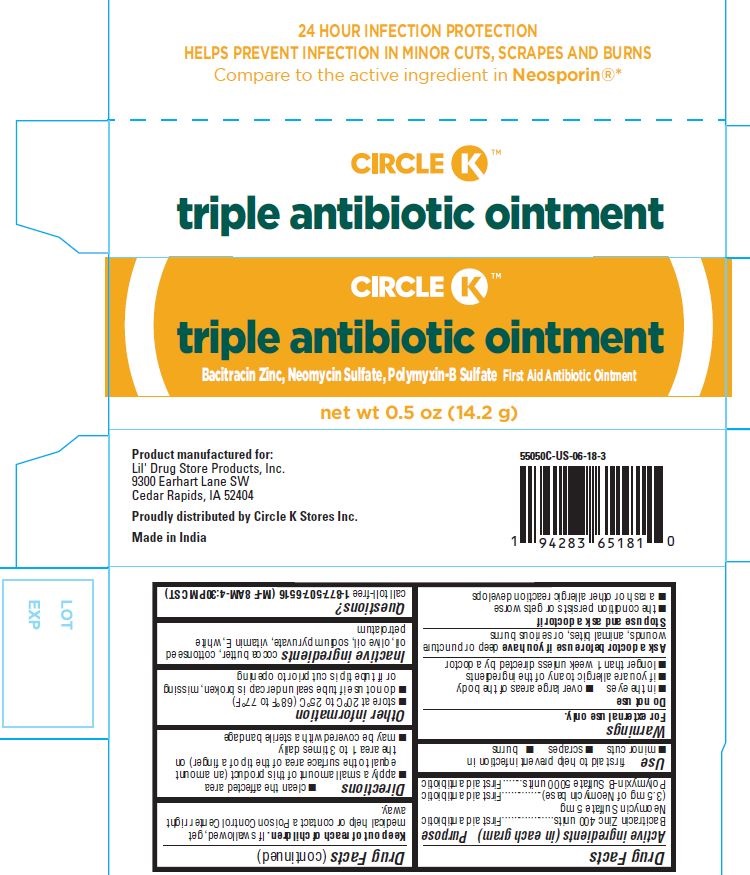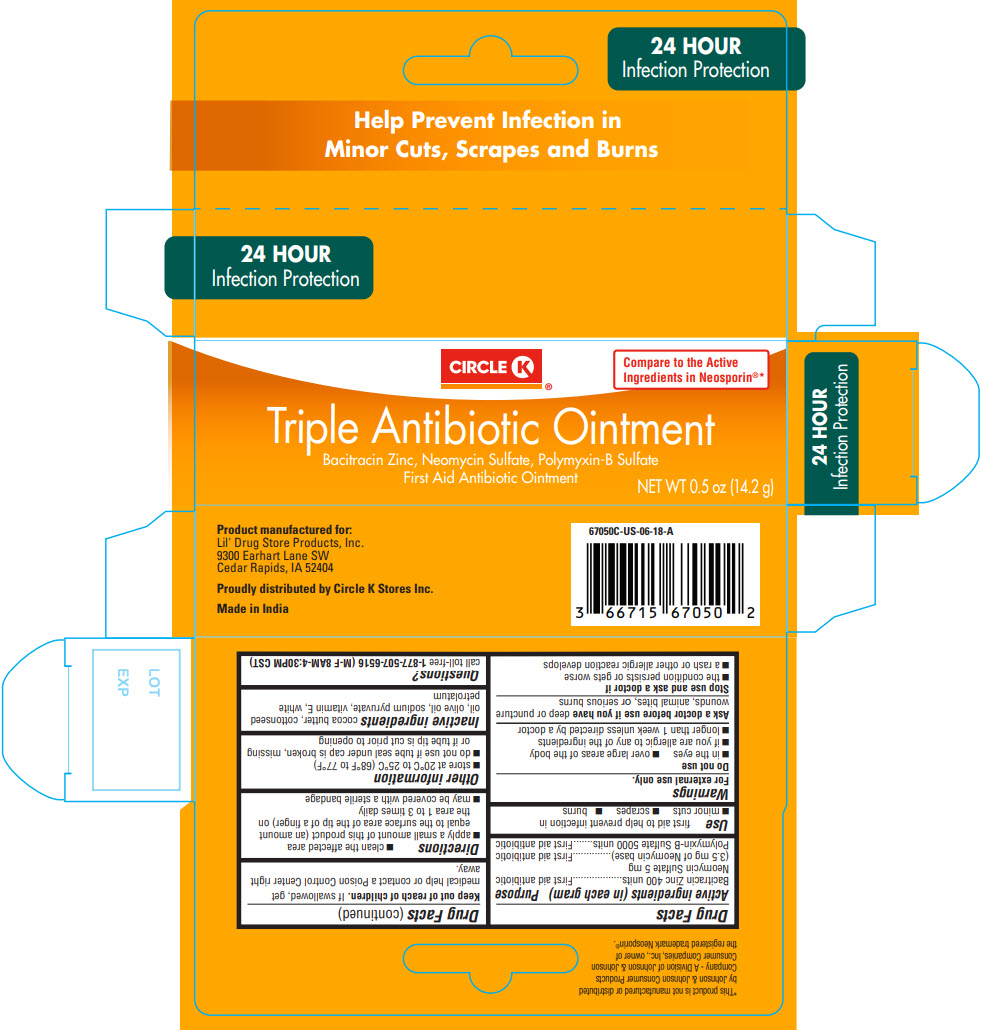 DRUG LABEL: Circle K Triple Antibiotic
NDC: 66715-5505 | Form: OINTMENT
Manufacturer: Lil Drug Store Products, Inc
Category: otc | Type: HUMAN OTC DRUG LABEL
Date: 20250702

ACTIVE INGREDIENTS: BACITRACIN ZINC 400 [iU]/1 1; POLYMYXIN B SULFATE 5000 [iU]/1 1; NEOMYCIN SULFATE 3.5 mg/1 1
INACTIVE INGREDIENTS: PETROLATUM; SODIUM PYRUVATE; COTTONSEED OIL; COCOA BUTTER; OLIVE OIL; ALPHA-TOCOPHEROL ACETATE

Circle K® Triple Antibiotic Ointment

Drug Facts

ACTIVE INGREDIENT

Active ingredients (in each gram) | Purpose
Bacitracin Zinc 400 units | First aid antibiotic
Neomycin Sulfate 5 mg (3.5 mg of Neomycin base) | First aid antibiotic
Polymyxin-B Sulfate 5000 units | First aid antibiotic

Use

first aid to help prevent infection in

- minor cuts
- scrapes
- burns

Warnings

For external use only.

Do not use

- in the eyes
- over large areas of the body
- if you are allergic to any of the ingredients
- longer than 1 week unless directed by a doctor

Ask a doctor before use if you have deep or puncture wounds, animal bites, or serious burns

Stop use and ask a doctor if

- the condition persists or gets worse
- a rash or other allergic reaction develops

Keep out of reach of children. If swallowed, get medical help or contact a Poison Control Center right away.

Directions

- clean the affected area
- apply a small amount of this product (an amount equal to the surface area of the tip of a finger) on the area 1 to 3 times daily
- may be covered with a sterile bandage

Other information

- store at 20°C to 25°C (68°F to 77°F)
- do not use if tube seal under cap is broken, missing or if tube tip is cut prior to opening

Inactive ingredients

cocoa butter, cottonseed oil, olive oil, sodium pyruvate, vitamin E, white petrolatum

Questions?

call toll-free 1-877-507-6516 (M-F 8AM-4:30PM CST)

Proudly distributed by Circle K Stores Inc.

PRINCIPAL DISPLAY PANEL - 14.2 g Tube Carton

24 HOUR
Infection Protection

Help Prevent Infection in
Minor Cuts, Scrapes and Burns

CIRCLE K®

Compare to the Active
Ingredients in Neosporin®*

Triple Antibiotic Ointment
Bacitracin Zinc, Neomycin Sulfate, Polymyxin-B Sulfate
First Aid Antibiotic Ointment

NET WT 0.5 oz (14.2 g)

PDP/Package - NDC 66715-5505

CIRCLE K™

triple antibiotic ointment

Bacitracin Zinc, Neomycin Sulfate, Polymyxin-B Sulfate First Aid Antibiotic Ointment

net wt 0.5 oz (14.2 g)